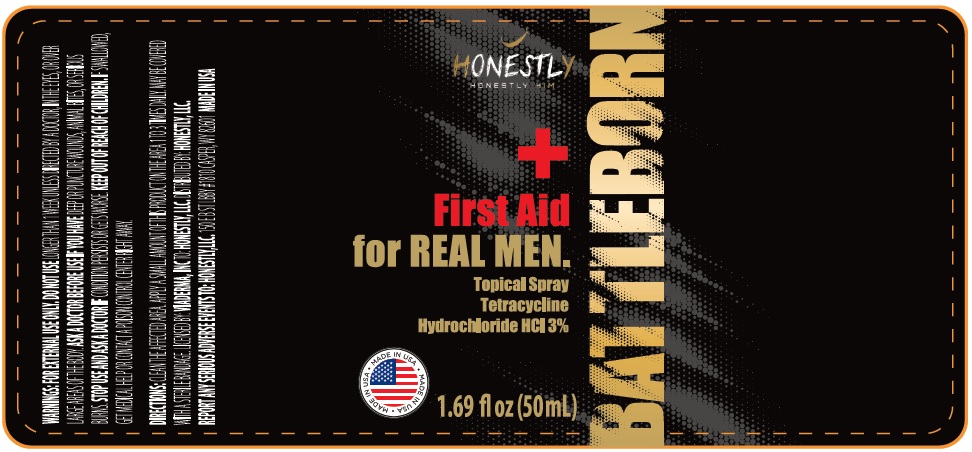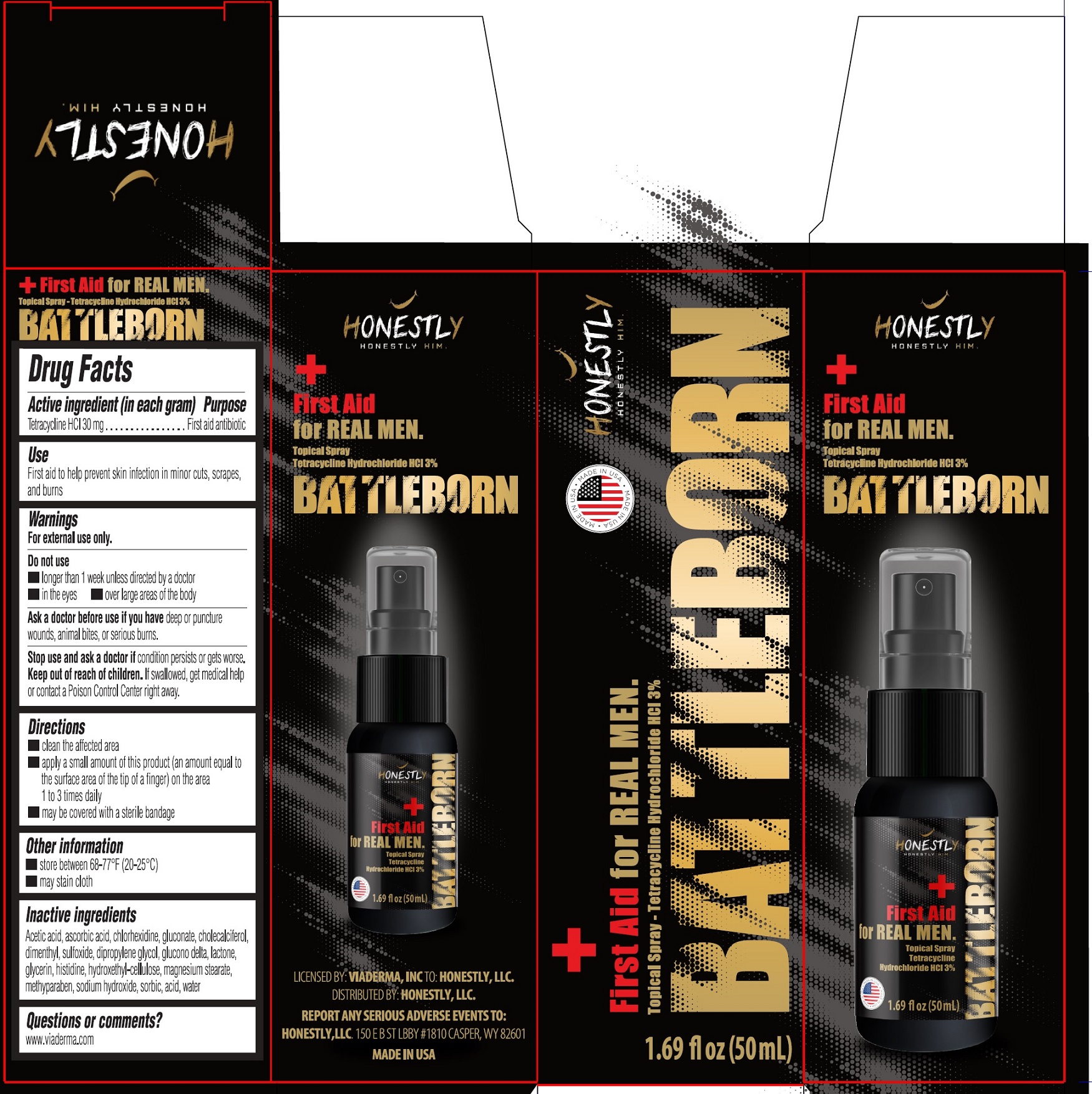 DRUG LABEL: Honestly Battleborn First Aid for Real Man
NDC: 85494-000 | Form: SPRAY
Manufacturer: HONESTLY LLC
Category: otc | Type: HUMAN OTC DRUG LABEL
Date: 20250407

ACTIVE INGREDIENTS: TETRACYCLINE HYDROCHLORIDE 30 mg/1 mL
INACTIVE INGREDIENTS: ACETIC ACID; ASCORBIC ACID; CHLORHEXIDINE; GLUCONATE ION; CHOLECALCIFEROL; ISOSAFROLE OCTYL SULFOXIDE; DIPROPYLENE GLYCOL; GLUCONOLACTONE; GLYCERIN; HISTIDINE; HYDROXYETHYL CELLULOSE, UNSPECIFIED; MAGNESIUM STEARATE; METHYLPARABEN; SODIUM HYDROXIDE; SORBIC ACID; WATER

Honestly Battleborn First Aid for Real Man Topical Spray

Active ingredient (in each gram)

Tetracycline HCl 30 mg

Purpose

First aid antibiotic

Use

First aid to help prevent skin infection in minor cuts, scrapes, and burns

Warnings

For external use only.

Do not use

- longer than 1 week unless directed by a doctor
- in the eyes
- over large areas of the body

Ask a doctor before use if you have

deep or puncture wounds, animal bites, or serious burns.

Stop use and ask a doctor if

condition persists or gets worse.

Keep out of reach of children.

If swallowed, get medical help or contact a Poison Control Center right away.

Directions

- clean the affected area
- apply a small amount of this product (an amount equal to the surface area of the tip of a finger) on the area 1 to 3 times daily
- may be covered with a sterile bandage

Other information

- store between 68-77°F (20-25°C)
- may stain cloth

Inactive ingredients

Acetic acid, ascorbic acid, chlorhexidine, gluconate, cholecalciferol, dimethyl, sulfoxide, dipropylene glycol, glucono delta, lactone, glycerin, histidine, hydroxethyl-cellulose, magnesium stearate, methylparaben, sodium hydroxide, sorbic acid, water

Questions or comments?

www.viadermainc.com